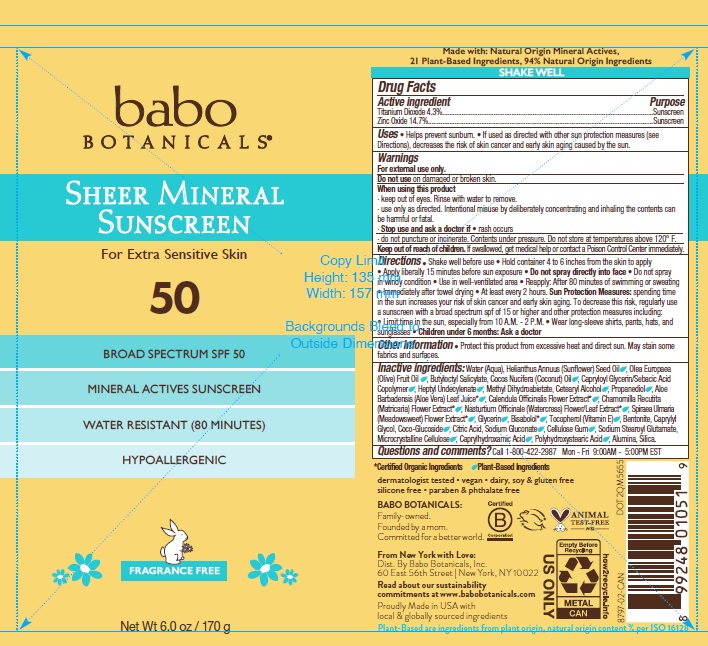 DRUG LABEL: SPF 50 Sheer Mineral Sensitive Sunscreen
NDC: 79265-8797 | Form: AEROSOL, SPRAY
Manufacturer: Babo Botanicals, Inc.
Category: otc | Type: HUMAN OTC DRUG LABEL
Date: 20241212

ACTIVE INGREDIENTS: ZINC OXIDE 15 g/100 mL; TITANIUM DIOXIDE 4.65 g/100 mL
INACTIVE INGREDIENTS: WATER; BUTYLOCTYL SALICYLATE; CARBOXYMETHYLCELLULOSE SODIUM, UNSPECIFIED FORM; CITRIC ACID MONOHYDRATE; COCO GLUCOSIDE; GLYCERIN; HEPTYL UNDECYLENATE; NASTURTIUM OFFICINALE FLOWERING TOP; SODIUM GLUCONATE; CAPRYLHYDROXAMIC ACID; CAPRYLYL GLYCOL; LEVOMENOL; SILICON DIOXIDE; SODIUM STEAROYL GLUTAMATE; ALOE VERA LEAF; METHYL DIHYDROABIETATE; POLYHYDROXYSTEARIC ACID (2300 MW); FILIPENDULA ULMARIA FLOWER; ALUMINUM OXIDE; BENTONITE; CALENDULA OFFICINALIS FLOWER; CAPRYLOYL GLYCERIN/SEBACIC ACID COPOLYMER (2000 MPA.S); CHAMOMILE; COCONUT OIL; CELLULOSE, MICROCRYSTALLINE; OLIVE OIL; PROPANEDIOL; CETOSTEARYL ALCOHOL; SUNFLOWER OIL; TOCOPHEROL

8797 Babo SPF 50 Sheer Sunscreen Spray

Active ingredients

Titanium Dioxide 4.3%
Zinc Oxide 14.7%

Purpose

Sunscreen

Uses

- Helps prevent sunburn.
- If used as directed with other sun protection measures (see Directions), decreases the risk of skin cancer and early skin aging caused by the sun.

Warnings

For external use only.

Do not use

on damaged or broken skin

When using this product

- keep out of eyes. Rinse with water to remove.
- use only as directed. Intentional misuse by deliberately concentrating and inhaling the contents can be harmful or fatal.

Stop use and ask doctor if

- rash occurs
- do not puncture or incinerate. Contents under pressure. Do not store at temperatures above 120° F.

Keep out of reach of children.

If swallowed, get medical help or contact a Poison Control Center immediately

Directions

• Shake well before use • Hold container 4 to 6 inches from the skin to apply • Apply liberally 15 minutes before sun exposure • Do not spray directly into face • Do not spray in windy condition • Use in well-ventilated area • Reapply: After 80 minutes of swimming or sweating • Immediately after towel drying • At least every 2 hours. Sun Protection Measures: spending time in the sun increases your risk of skin cancer and early skin aging. To decrease this risk, regularly use a sunscreen with a broad spectrum spf of 15 or higher and other protection measures including: • Limit time in the sun, especially from 10 A.M. - 2 P.M. • Wear long-sleeve shirts, pants, hats, and sunglasses • Children under 6 months: Ask a doctor

Other Information

• Protect this product from excessive heat and direct sun. May stain some fabrics and surfaces.

Inactive ingredients

Water (Aqua), Helianthus Annuus (Sunflower) Seed Oil, Olea Europaea (Olive) Fruit Oil, Butyloctyl Salicylate, Cocos Nucifera (Coconut) Oil, Capryloyl Glycerin/Sebacic Acid Copolymer, Heptyl Undecylenate, Methyl Dihydroabietate, Cetearyl Alcohol, Propanediol, Aloe Barbadensis (Aloe Vera) Leaf Juice*, Calendula Officinalis Flower Extract*, Chamomilla Recutita (Matricaria) Flower Extract*, Nasturtium Officinale (Watercress) Flower/Leaf Extract*, Spiraea Ulmaria (Meadowsweet) Flower Extract*, Glycerin, Bisabolol*, Tocopherol (Vitamin E), Bentonite, Caprylyl Glycol, Coco-Glucoside, Citric Acid, Sodium Gluconate, Cellulose Gum, Sodium Stearoyl Glutamate, Microcrystalline Cellulose, Caprylhydroxamic Acid, Polyhydroxystearic Acid, Alumina, Silica.
*Certified Organic Ingredients

Questions and comments?

Call 1-800-422-2987 Mon - Fri 9:00AM - 5:00PM EST